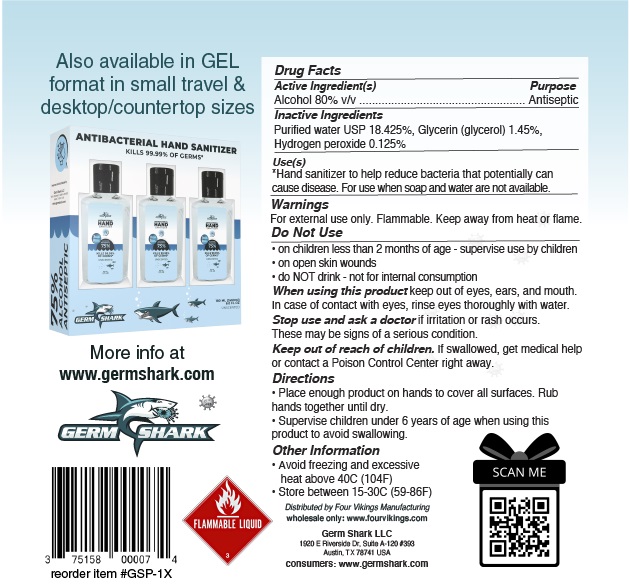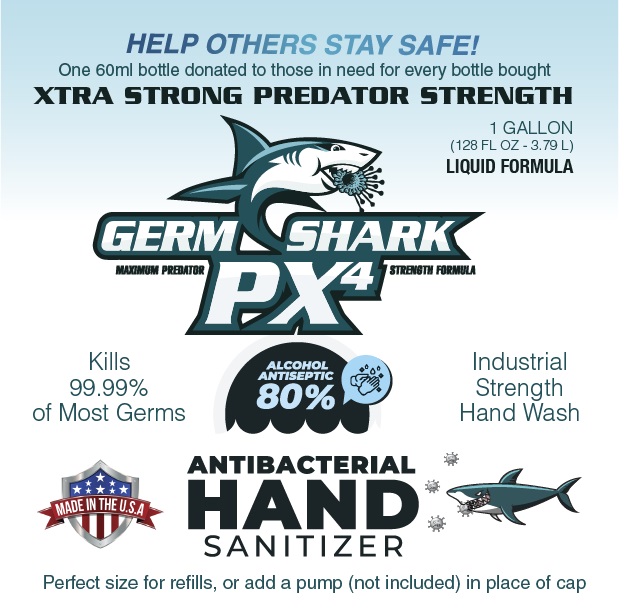 DRUG LABEL: Germ Shark PX4 Hand Sanitizer
NDC: 75158-002 | Form: LIQUID
Manufacturer: Germ Shark LLC
Category: otc | Type: HUMAN OTC DRUG LABEL
Date: 20200816

ACTIVE INGREDIENTS: ALCOHOL 0.8 mL/1 mL
INACTIVE INGREDIENTS: WATER; GLYCERIN; HYDROGEN PEROXIDE

Germ Shark PX4 Hand Sanitizer

Active Ingredient(s)

Alcohol 80% v/v

Purpose

Antiseptic

Inactive Ingredients

Purified water USP 18.425%, Glycerin (glycerol) 1.45%, Hydrogen peroxide 0.125%

Use(s)

Hand sanitizer to help reduce bacteria that potentially can cause disease. For use when soap and water are not available.

Warnings

For external use only. Flammable. Keep away from heat or flame.

Do Not Use

- on children less than 2 months of age- supervise use by children
- on open skin wounds
- do NOT drink - not for internal consumption

When using this product

keep out of eyes, ears, and mouth. In case of contact with eyes, rinse eyes thoroughly with water.

Stop use and ask a doctor

if irritation or rash occurs. These may be signs of a serious condition.

Keep out of reach of children.

If swallowed, get medical help or contact a Poison Control Center right away.

Directions

- Place enough product on hands to cover all surfaces. Rub hands together until dry.
- Supervise children under 6 years of age when using this product to avoid swallowing.

Other Information

- Avoid freezing and excessive heat above 40C (104F)
- Store between 15-30C (59-86F)